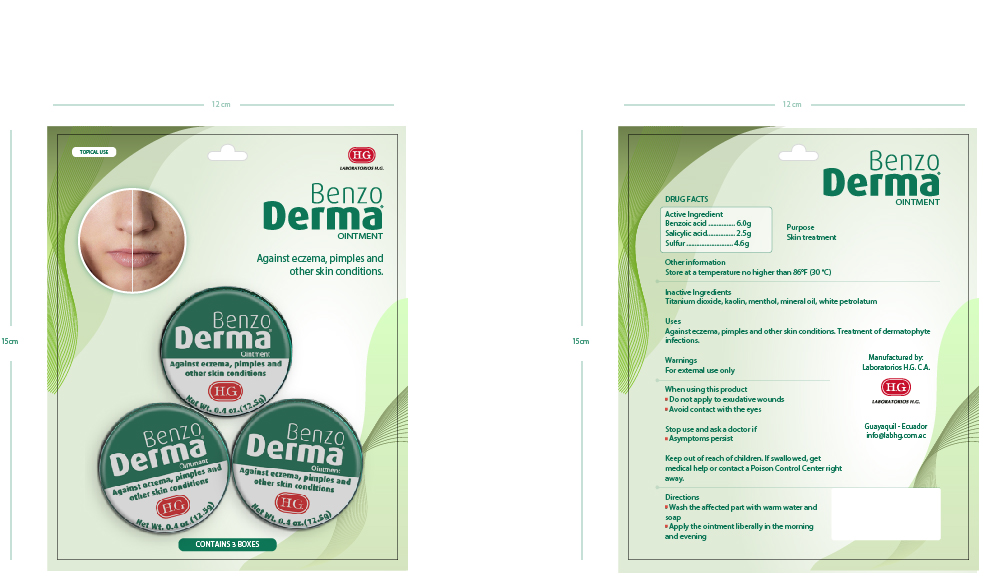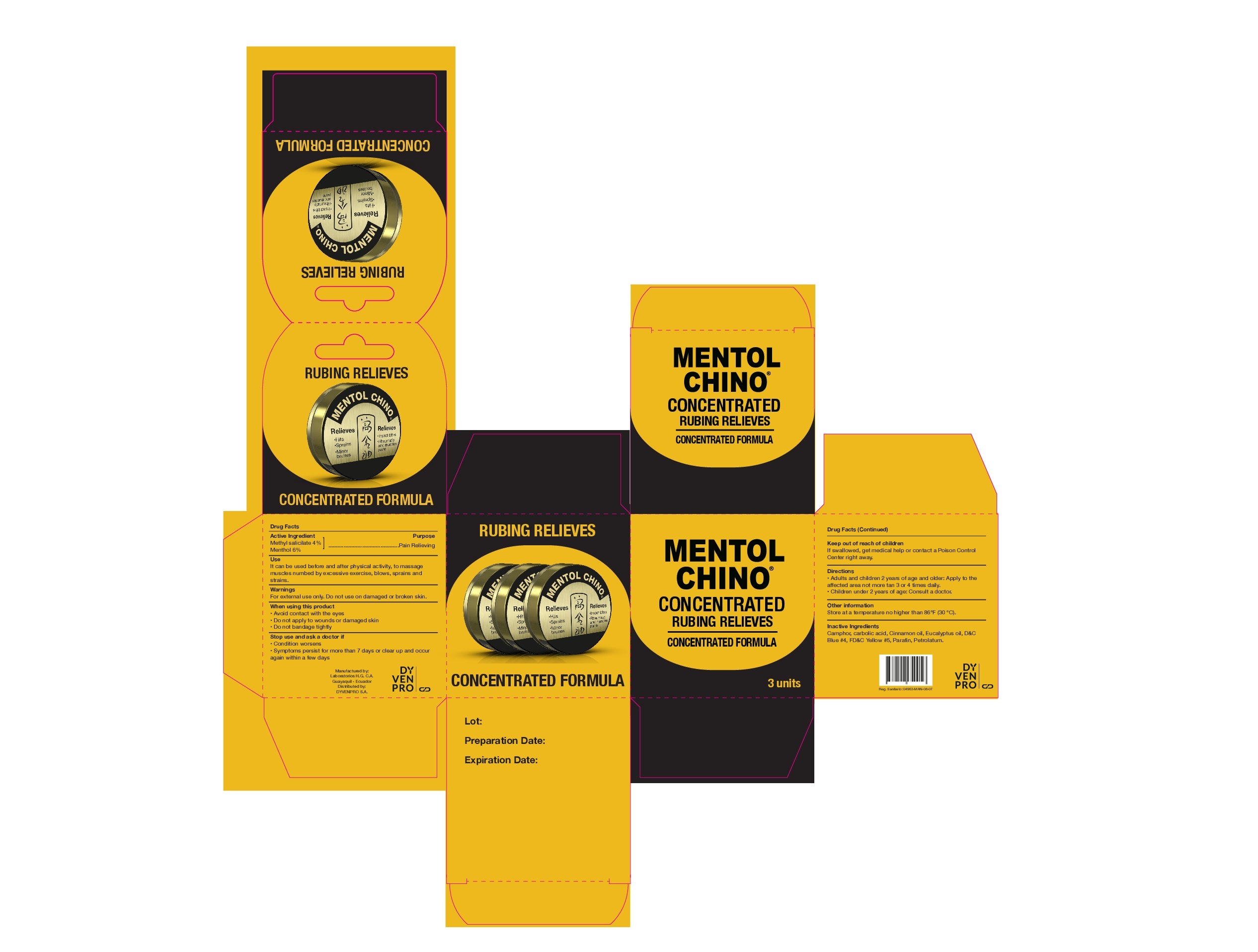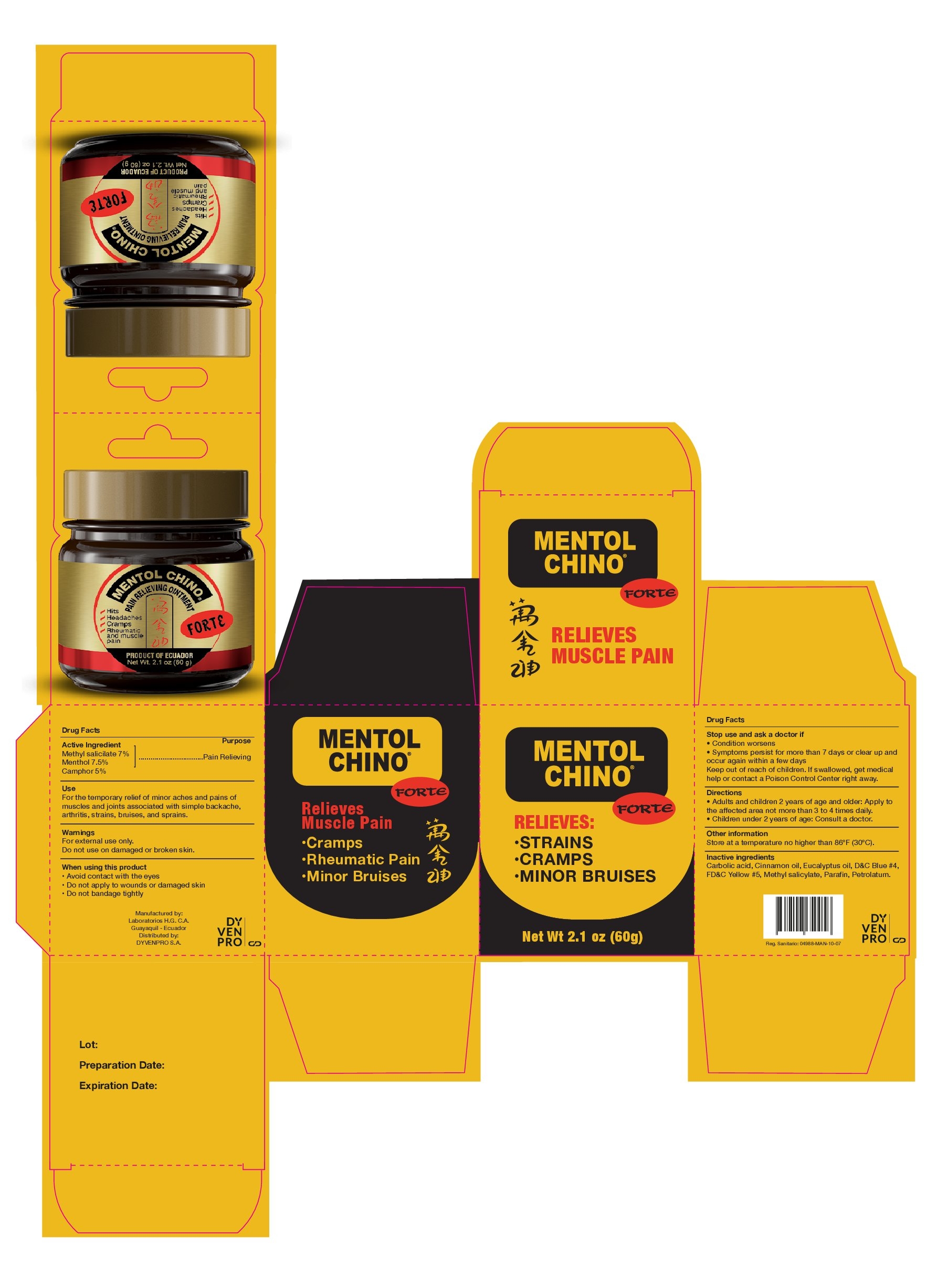 DRUG LABEL: MENTOL CHINO CONCENTRATED
NDC: 84058-120 | Form: CREAM
Manufacturer: LABORATORIOS H.G. C.A.
Category: otc | Type: HUMAN OTC DRUG LABEL
Date: 20240227

ACTIVE INGREDIENTS: METHYL SALICYLATE 4 g/100 g; MENTHOL 6 g/100 g
INACTIVE INGREDIENTS: EUCALYPTUS RADIATA LEAF OIL 0.45 g/100 g; CAMPHOR OIL 4 g/100 g; FD&C YELLOW NO. 5 0.0003 g/100 g; PETROLATUM 80 g/100 g; CINNAMON OIL 0.25 g/100 g; PHENOL 0.45 g/100 g; D&C BLUE NO. 4 0.0013 g/100 g; PARAFFIN 4 g/100 g

INDICATIONS AND USAGE

AGAINST ECZEMA, PIMPLES AND OTHER SKIN CONDITIONS

ACTIVE INGREDIENTS

BENZOIC ACID 6.0 g, SALYCYLIC ACID 2.5 g, SULFUR 4.6 g

PURPOSE

SKIN TREATMENT

USES

AGAINST ECZEMA, PIMPLES AND OTHER SKIN CONDITIONS. TREATMENT OF DERMATOPHYTE INFECTIONS.

WARNINGS

FOR EXTERNAL USE ONLY.

WHEN USING THIS PRODUCT

DO NOT APPLY TO EXUDATIVE WOUNDS.

AVOID CONTACT WITH EYES.

STOP USE AND ASK A DOCTOR IF

SYMPTOMS PERSIST

KEEP OUT OF REACH OF CHILDREN

IF SWALLOWED, GET MEDICAL HELP OR CONTACT A POISON CONTROL CENTER RIGHT AWAY.

DIRECTIONS

WASH THE AFFECT PART WITH WARM WATER AND SOAP.

APPLY THE OINMENT LIBERALLY IN THE MORNING AND EVENING.

OTHER INFORMATION

STORE AT TEMPERATURE NOT HIGHER THAN 86°F (30°C).

INACTIVE INGREDIENTS

TITANIUM DIOXIDE, KAOLIN, MENTHOL, MINERAL OIL, WHITE PETROLATUM.